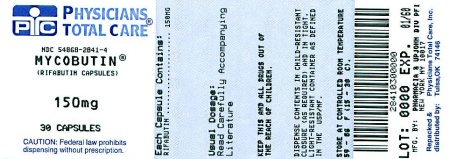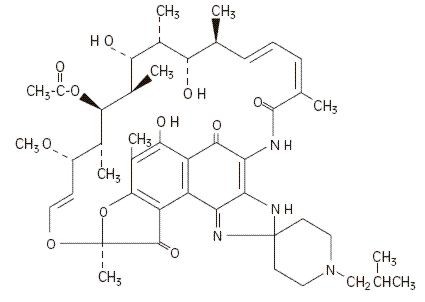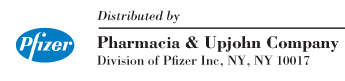 DRUG LABEL: Mycobutin
NDC: 54868-2841 | Form: CAPSULE
Manufacturer: Physicians Total Care, Inc.
Category: prescription | Type: HUMAN PRESCRIPTION DRUG LABEL
Date: 20100604

ACTIVE INGREDIENTS: RIFABUTIN 150 mg/1 1
INACTIVE INGREDIENTS: CELLULOSE, MICROCRYSTALLINE; MAGNESIUM STEARATE; FERRIC OXIDE RED; SILICON DIOXIDE; SODIUM LAURYL SULFATE; TITANIUM DIOXIDE

Mycobutin®
rifabutin capsules, USP

DESCRIPTION

MYCOBUTIN Capsules contain the antimycobacterial agent rifabutin, which is a semisynthetic ansamycin antibiotic derived from rifamycin S. MYCOBUTIN Capsules for oral administration contain 150 mg of rifabutin, USP, per capsule, along with the inactive ingredients microcrystalline cellulose, magnesium stearate, red iron oxide, silica gel, sodium lauryl sulfate, titanium dioxide, and edible white ink.

The chemical name for rifabutin is 1',4-didehydro-1-deoxy-1,4-dihydro-5'-(2-methylpropyl)-1-oxorifamycin XIV (Chemical Abstracts Service, 9th Collective Index) or (9S, 12E, 14S, 15R, 16S, 17R, 18R, 19R, 20S, 21S, 22E, 24Z)-6,16,18,20-tetrahydroxy-1'-isobutyl-14-methoxy-7,9,15,17,19,21,25-heptamethyl-spiro [9,4-(epoxypentadeca[1,11,13]trienimino)-2H-furo[2',3':7,8]naphth[1,2-d] imidazole-2,4'-piperidine]-5,10,26-(3H,9H)-trione-16-acetate. Rifabutin has a molecular formula of C46H62N4O11, a molecular weight of 847.02 and the following structure:

Rifabutin is a red-violet powder soluble in chloroform and methanol, sparingly soluble in ethanol, and very slightly soluble in water (0.19 mg/mL). Its log P value (the base 10 logarithm of the partition coefficient between n-octanol and water) is 3.2 (n-octanol/water).

CLINICAL PHARMACOLOGY

Pharmacokinetics

Absorption

Following a single oral dose of 300 mg to nine healthy adult volunteers, rifabutin was readily absorbed from the gastrointestinal tract with mean (±SD) peak plasma levels (Cmax) of 375 (±267) ng/mL (range: 141 to 1033 ng/mL) attained in 3.3 (±0.9) hours (Tmax range: 2 to 4 hours). Absolute bioavailability assessed in five HIV-positive patients, who received both oral and intravenous doses, averaged 20%. Total recovery of radioactivity in the urine indicates that at least 53% of the orally administered rifabutin dose is absorbed from the gastrointestinal tract. The bioavailability of rifabutin from the capsule dosage form, relative to an oral solution, was 85% in 12 healthy adult volunteers. High-fat meals slow the rate without influencing the extent of absorption from the capsule dosage form. Plasma concentrations post-Cmax declined in an apparent biphasic manner. Pharmacokinetic dose-proportionality was established over the 300 to 600 mg dose range in nine healthy adult volunteers (crossover design) and in 16 early symptomatic human immunodeficiency virus (HIV)-positive patients over a 300 to 900 mg dose range.

Distribution

Due to its high lipophilicity, rifabutin demonstrates a high propensity for distribution and intracellular tissue uptake. Following intravenous dosing, estimates of apparent steady-state distribution volume (9.3 ± 1.5 L/kg) in five HIV-positive patients exceeded total body water by approximately 15-fold. Substantially higher intracellular tissue levels than those seen in plasma have been observed in both rat and man. The lung-to-plasma concentration ratio, obtained at 12 hours, was approximately 6.5 in four surgical patients who received an oral dose. Mean rifabutin steady-state trough levels (Cp,minss; 24-hour post-dose) ranged from 50 to 65 ng/mL in HIV-positive patients and in healthy adult volunteers. About 85% of the drug is bound in a concentration-independent manner to plasma proteins over a concentration range of 0.05 to 1 µg/mL. Binding does not appear to be influenced by renal or hepatic dysfunction. Rifabutin was slowly eliminated from plasma in seven healthy adult volunteers, presumably because of distribution-limited elimination, with a mean terminal half-life of 45 (±17) hours (range: 16 to 69 hours). Although the systemic levels of rifabutin following multiple dosing decreased by 38%, its terminal half-life remained unchanged.

Metabolism

Of the five metabolites that have been identified, 25-O-desacetyl and 31-hydroxy are the most predominant, and show a plasma metabolite:parent area under the curve ratio of 0.10 and 0.07, respectively. The former has an activity equal to the parent drug and contributes up to 10% to the total antimicrobial activity.

Excretion

A mass-balance study in three healthy adult volunteers with ^14C-labeled rifabutin showed that 53% of the oral dose was excreted in the urine, primarily as metabolites. About 30% of the dose is excreted in the feces. Mean systemic clearance (CLs/F) in healthy adult volunteers following a single oral dose was 0.69 (±0.32) L/hr/kg (range: 0.46 to 1.34 L/hr/kg). Renal and biliary clearance of unchanged drug each contribute approximately 5% to CLs/F.

Pharmacokinetics in Special Populations

Geriatric

Compared to healthy volunteers, steady-state kinetics of MYCOBUTIN are more variable in elderly patients (>70 years).

Pediatric

The pharmacokinetics of MYCOBUTIN have not been studied in subjects under 18 years of age.

Renal Insufficiency

The disposition of rifabutin (300 mg) was studied in 18 patients with varying degrees of renal function. Area under plasma concentration time curve (AUC) increased by about 71% in patients with severe renal insufficiency (creatinine clearance below 30 mL/min) compared to patients with creatinine clearance (Crcl) between 61–74 mL/min. In patients with mild to moderate renal insufficiency (Crcl between 30–61 mL/min), the AUC increased by about 41%. A reduction in the dosage of rifabutin is recommended for patients with Crcl< 30 mL/min (see DOSAGE AND ADMINISTRATION).

Drug-Drug Interactions

(see also PRECAUTIONS-Drug Interactions)

Rifabutin induces the enzymes of the cytochrome P450 3A subfamily (CYP3A) and therefore may reduce the plasma concentrations of drugs that are principally metabolized by those enzymes. Rifabutin is also metabolized by CYP3A. Thus, some drugs that inhibit CYP3A may significantly increase plasma concentrations of rifabutin.

Antifungals

Fluconazole

Fluconazole (200 mg/day for 2 weeks) increased the AUC of rifabutin (300 mg/day for 2 weeks) by 82% and Cmax by 88% in 12 HIV-infected patients who were on zidovudine (500 mg/day) maintenance therapy (see PRECAUTIONS-Drug Interactions). Rifabutin did not affect the pharmacokinetics of fluconazole.

Itraconazole

Coadministration of itraconazole (200 mg/day) with rifabutin (300 mg/day) in six HIV-infected patients reduced both the AUC and Cmax of itraconazole by 70% to 75% (see PRECAUTIONS-Drug Interactions).

Antipneumocystis Agents

Dapsone

Rifabutin (300 mg/day) decreased the AUC of dapsone (50 mg/day) in HIV-infected patients (n=16) by about 27% to 40%.

Sulfamethoxazole-trimethoprim

Coadministration of rifabutin (300 mg/day) and sulfamethoxazole-trimethoprim (double strength) in 12 HIV-infected patients decreased the AUC of sulfamethoxazole-trimethoprim by about 15% to 20%. When trimethoprim was given alone, the AUC of trimethoprim was decreased by 14% and the Cmax by 6%.

Sulfamethoxazole-trimethoprim did not alter the pharmacokinetics of rifabutin.

Antiretroviral Agents

Delavirdine

In 7 HIV-infected patients, rifabutin (300 mg/day) decreased delavirdine (400 mg q 8h) AUC by about 80%, Cmax by about 75%, and mean trough plasma concentrations by about 95%. Based on comparisons with historical data, delavirdine appeared to increase the AUC of rifabutin by at least 100% (see PRECAUTIONS-Drug Interactions).

Didanosine

In 12 HIV-infected patients, coadministration of rifabutin (300 or 600 mg/day) and didanosine (167–375 mg BID) did not alter the pharmacokinetics of either drug.

Indinavir

In healthy volunteers, coadministration of indinavir (800 mg q 8h) and rifabutin (300 mg/day) decreased the AUC of indinavir by about 30% and increased the AUC of rifabutin by about 200% (see PRECAUTIONS-Drug Interactions).

Nelfinavir

Coadministration of nelfinavir (750 mg q 8h for 8 days) and rifabutin (300 mg/day for 7–8 days) decreased the AUC and Cmax of nelfinavir by about 32% and 25%, respectively, and increased the AUC and Cmax of rifabutin by about 207% and 146%, respectively (see PRECAUTIONS-Drug Interactions).

Ritonavir

Coadministration of ritonavir (500 mg q 12h) and rifabutin (150 mg/day) increased the AUC and Cmax of rifabutin by more than 400% and 250%, respectively (see PRECAUTIONS-Drug Interactions).

Saquinavir

In 12 HIV-infected patients, rifabutin (300 mg/day) decreased the AUC of saquinavir (600 mg TID) by about 40% (see PRECAUTIONS-Drug Interactions).

Zidovudine

In 16 HIV-infected patients on zidovudine (100 or 200 mg q 4h), rifabutin (300 or 450 mg/day) lowered the Cmax and AUC of zidovudine by about 48% and 32%, respectively. However, zidovudine levels remained within the therapeutic range during coadministration of rifabutin. Zidovudine did not affect the pharmacokinetics of rifabutin.

Antituberculosis Agents

In studies conducted in healthy volunteers, rifabutin (300 mg) did not alter the pharmacokinetics of ethambutol (n=10) or isoniazid (n=10).

Macrolides

Clarithromycin

In studies conducted in HIV-infected patients, coadministration of rifabutin (300 mg/day) and clarithromycin (500 mg q 12h) decreased the AUC of clarithromycin by about 50% (n=12) and increased the AUC of rifabutin by about 75% (n=14) (see PRECAUTIONS-Drug Interactions).

Other Drugs

Methadone

Rifabutin did not alter the pharmacokinetics of methadone in 24 HIV-infected, methadone-maintained, former intravenous drug users.

Oral contraceptives

In 22 healthy female volunteers receiving an oral contraceptive (35 mcg ethinylestradiol (EE) and 1 mg norethindrone (NE) daily for 21 days), rifabutin decreased EE (AUC) and Cmax by 35% and 20%, respectively, and NE AUC by 46% (see PRECAUTIONS-Drug Interactions).

Theophylline

Rifabutin did not alter the pharmacokinetics of theophylline when coadministered in 11 healthy volunteers.

Other drugs

The structurally similar drug, rifampin, is known to reduce the plasma concentrations of a number of other drugs (see prescribing information for rifampin). Although rifabutin is a weaker enzyme inducer than rifampin, rifabutin may be expected to have some effect on those drugs as well.

CLINICAL STUDIES

Two randomized, double-blind clinical trials (study 023 and study 027) compared MYCOBUTIN (300 mg/day) to placebo in patients with CDC-defined AIDS and CD4 counts ≤ 200 cells/µL. These studies accrued patients from 2/90 through 2/92. Study 023 enrolled 590 patients, with a median CD4 cell count at study entry of 42 cells/µL (mean 61). Study 027 enrolled 556 patients with a median CD4 cell count at study entry of 40 cells/µL (mean 58).

Endpoints included the following:

(1) MAC bacteremia, defined as at least one blood culture positive for Mycobacterium avium complex (MAC) bacteria.
(2) Clinically significant disseminated MAC disease, defined as MAC bacteremia accompanied by signs or symptoms of serious MAC infection, including one or more of the following: fever, night sweats, rigors, weight loss, worsening anemia, and/or elevations in alkaline phosphatase.
(3) Survival

MAC bacteremia

Participants who received MYCOBUTIN were one-third to one-half as likely to develop MAC bacteremia as were participants who received placebo. These results were statistically significant (study 023: p<0.001; study 027: p = 0.002).

In study 023, the one-year cumulative incidence of MAC bacteremia, on an intent to treat basis, was 9% for patients randomized to MYCOBUTIN and 22% for patients randomized to placebo. In study 027, these rates were 13% and 28% for patients receiving MYCOBUTIN and placebo, respectively.

Most cases of MAC bacteremia (approximately 90% in these studies) occurred among participants whose CD4 count at study entry was ≤100 cells/µL. The median and mean CD4 counts at onset of MAC bacteremia were 13 cells/µL and 24 cells/µL, respectively. These studies did not investigate the optimal time to begin MAC prophylaxis.

Clinically significant disseminated MAC disease

In association with the decreased incidence of bacteremia, patients on MYCOBUTIN showed reductions in the signs and symptoms of disseminated MAC disease, including fever, night sweats, weight loss, fatigue, abdominal pain, anemia, and hepatic dysfunction.

Survival

The one-year survival rates in study 023 were 77% for the group receiving MYCOBUTIN and 77% for the placebo group. In study 027, the one-year survival rates were 77% for the group receiving MYCOBUTIN and 70% for the placebo group.

These differences were not statistically significant.

MICROBIOLOGY

Mechanism of Action

Rifabutin inhibits DNA-dependent RNA polymerase in susceptible strains of Escherichia coli and Bacillus subtilis but not in mammalian cells. In resistant strains of E. coli, rifabutin, like rifampin, did not inhibit this enzyme. It is not known whether rifabutin inhibits DNA-dependent RNA polymerase in Mycobacterium avium or in M. intracellulare which comprise M. avium complex (MAC).

Susceptibility Testing

In vitro susceptibility testing methods and diagnostic products used for determining minimum inhibitory concentration (MIC) values against M. avium complex (MAC) organisms have not been standardized. Breakpoints to determine whether clinical isolates of MAC and other mycobacterial species are susceptible or resistant to rifabutin have not been established.

In Vitro Studies

Rifabutin has demonstrated in vitro activity against M. avium complex (MAC) organisms isolated from both HIV-positive and HIV-negative people. While gene probe techniques may be used to identify these two organisms, many reported studies did not distinguish between these two species. The vast majority of isolates from MAC-infected, HIV-positive people are M. avium, whereas in HIV-negative people, about 40% of the MAC isolates are M. intracellulare.

Various in vitro methodologies employing broth or solid media, with and without polysorbate 80 (Tween 80), have been used to determine rifabutin MIC values for mycobacterial species. In general, MIC values determined in broth are several fold lower than that observed with methods employing solid media. Utilization of Tween 80 in these assays has been shown to further lower MIC values.

However, MIC values were substantially higher for egg-based compared to agar-based solid media.

Rifabutin activity against 211 MAC isolates from HIV-positive people was evaluated in vitro utilizing a radiometric broth and an agar dilution method. Results showed that 78% and 82% of these isolates had MIC99 values of ≤0.25 µg/mL and ≤1.0 µg/mL, respectively, when evaluated by these two methods. Rifabutin was also shown to be active against phagocytized, M. avium complex in a mouse macrophage cell culture model.

Rifabutin has in vitro activity against many strains of Mycobacterium tuberculosis. In one study, utilizing the radiometric broth method, each of 17 and 20 rifampin-naive clinical isolates tested from the United States and Taiwan, respectively, were shown to be susceptible to rifabutin concentrations of ≤0.125 µg/mL.

Cross-resistance between rifampin and rifabutin is commonly observed with M. tuberculosis and M. avium complex isolates. Isolates of M. tuberculosis resistant to rifampin are likely to be resistant to rifabutin. Rifampicin and rifabutin MIC99 values against 523 isolates of M. avium complex were determined utilizing the agar dilution method (Ref. Heifets, Leonid B. and Iseman, Michael D. 1985. Determination of in vitro susceptibility of Mycobacteria to Ansamycin. Am. Rev. Respir. Dis. 132 (3):710–711).

SUSCEPTIBILITY OF M. AVIUM COMPLEX STRAINS TO RIFAMPIN AND RIFABUTIN
 |  | % of Strains Susceptible/Resistant to Different Concentrations of Rifabutin (µg/mL)
Susceptibility to Rifampin (µg/mL) | Number of Strains | Susceptible to 0.5 | Resistant to 0.5 only | Resistant to 1.0 | Resistant to 2.0
Susceptible to 1.0 | 30 | 100.0 | 0.0 | 0.0 | 0.0
Resistant to 1.0 only | 163 | 88.3 | 11.7 | 0.0 | 0.0
Resistant to 5.0 | 105 | 38.0 | 57.1 | 2.9 | 2.0
Resistant to 10.0 | 225 | 20.0 | 50.2 | 19.6 | 10.2
TOTAL | 523 | 49.5 | 36.7 | 9.0 | 4.8

Rifabutin in vitro MIC99 values of ≤0.5 µg/mL, determined by the agar dilution method, for M. kansasii, M. gordonae and M. marinum have been reported; however, the clinical significance of these results is unknown.

INDICATIONS AND USAGE

MYCOBUTIN Capsules are indicated for the prevention of disseminated Mycobacterium avium complex (MAC) disease in patients with advanced HIV infection.

CONTRAINDICATIONS

MYCOBUTIN Capsules are contraindicated in patients who have had clinically significant hypersensitivity to rifabutin or to any other rifamycins.

WARNINGS

MYCOBUTIN Capsules must not be administered for MAC prophylaxis to patients with active tuberculosis. Tuberculosis in HIV-positive patients is common and may present with atypical or extrapulmonary findings. Patients are likely to have a nonreactive purified protein derivative (PPD) despite active disease. In addition to chest X-ray and sputum culture, the following studies may be useful in the diagnosis of tuberculosis in the HIV-positive patient: blood culture, urine culture, or biopsy of a suspicious lymph node.

When MYCOBUTIN is used concomitantly with clarithromycin for MAC treatment, a decreased dose of MYCOBUTIN is recommended due to the increase in plasma concentrations of MYCOBUTIN (see PRECAUTIONS-Drug Interactions). Due to the possible occurrence of uveitis, patients should also be carefully monitored when MYCOBUTIN is given in combination with clarithromycin (or other macrolides) and/or fluconazole (and related compounds). If uveitis is suspected, the patient should be referred to an ophthalmologist and, if considered necessary, treatment with MYCOBUTIN should be suspended (see also ADVERSE REACTIONS).

Patients who develop complaints consistent with active tuberculosis while on prophylaxis with MYCOBUTIN should be evaluated immediately, so that those with active disease may be given an effective combination regimen of anti-tuberculosis medications. Administration of MYCOBUTIN as a single agent to patients with active tuberculosis is likely to lead to the development of tuberculosis that is resistant both to MYCOBUTIN and to rifampin.

There is no evidence that MYCOBUTIN is effective prophylaxis against M. tuberculosis. Patients requiring prophylaxis against both M. tuberculosis and Mycobacterium avium complex may be given isoniazid and MYCOBUTIN concurrently.

Clostridium difficile associated diarrhea (CDAD) has been reported with use of nearly all antibacterial agents, including MYCOBUTIN (rifabutin capsules, USP), and may range in severity from mild diarrhea to fatal colitis. Treatment with antibacterial agents alters the normal flora of the colon leading to overgrowth of C. difficile.

C. difficile produces toxins A and B which contribute to the development of CDAD. Hypertoxin producing strains of C. difficile cause increased morbidity and mortality, as these infections can be refractory to antimicrobial therapy and may require colectomy. CDAD must be considered in all patients who present with diarrhea following antibiotic use. Careful medical history is necessary since CDAD has been reported to occur over two months after the administration of antibacterial agents.

If CDAD is suspected or confirmed, ongoing antibiotic use not directed against C. difficile may need to be discontinued. Appropriate fluid and electrolyte management, protein supplementation, antibiotic treatment of C. difficile, and surgical evaluation should be instituted as clinically indicated.

In accordance with the commonly accepted criteria for the treatment of mycobacterial infections, MYCOBUTIN should always be given in combination with other anti-mycobacterial drugs not belonging to the family of rifamycins.

For patients with severe liver insufficiency a dose reduction should be considered. Mild hepatic impairment does not require a dose modification.

Severe renal impairment (creatinine clearance below 30 mL/min) requires a dosage reduction of 50%. Mild to moderate renal impairment does not require any dosage adjustment.

Protease inhibitors act as substrates or inhibitors of CYP450 IIIA4 mediated metabolism. Therefore, due to significant drug-drug interactions between protease inhibitors and rifabutin, their concomitant use should be based on the overall assessment of the patient and a patient-specific drug profile (see PRECAUTIONS-Drug Interactions). For further recommendations regarding protease inhibitors, please refer to current, official product monographs or contact the specific manufacturer.

PRECAUTIONS

General

Because treatment with MYCOBUTIN Capsules may be associated with neutropenia, and more rarely thrombocytopenia, physicians should consider obtaining hematologic studies periodically in patients receiving prophylaxis with MYCOBUTIN.

Information for Patients

Patients should be advised of the signs and symptoms of both MAC and tuberculosis, and should be instructed to consult their physicians if they develop new complaints consistent with either of these diseases. In addition, since MYCOBUTIN may rarely be associated with myositis and uveitis, patients should be advised to notify their physicians if they develop signs or symptoms suggesting either of these disorders.

Urine, feces, saliva, sputum, perspiration, tears, and skin may be colored brown-orange with rifabutin and some of its metabolites. Soft contact lenses may be permanently stained. Patients to be treated with MYCOBUTIN should be made aware of these possibilities.

Diarrhea is a common problem caused by antibiotics which usually ends when the antibiotic is discontinued. Sometimes, after starting treatment with antibiotics, patients can develop watery and bloody stools (with or without stomach cramps and fever) even as late as two or more months after having taken the last dose of the antibiotic. If this occurs, patients should contact their physician as soon as possible.

There is no reason to believe that MYCOBUTIN has any adverse effect on the ability to drive and/or use machines.

Drug Interactions

Multiple dosing of rifabutin has been associated with induction of hepatic metabolic enzymes of the CYP450 IIIA subfamily. Rifabutin's predominant metabolite (25-desacetyl rifabutin; LM 565), may also contribute to this effect. Metabolic induction due to rifabutin is likely to produce a decrease in circulating levels of concomitantly administered drugs (especially those metabolized by the CYP450 IIIA pathway). Kinetic data suggest that enzymatic induction by rifabutin is complete within 5 days and is dose-independent over the 300 to 600 mg dose-range. Similarly, concomitant medications that competitively inhibit the CYP450 IIIA activity may increase circulating levels of rifabutin.

Malabsorption

Gastric pH alteration due to progressing HIV disease has been linked with malabsorption of some drugs used in HIV-positive patients (e.g., rifampin, isoniazid). Drug serum concentration data from AIDS patients with varying disease severity (based on CD4+ counts) suggest that rifabutin absorption is not influenced by progressing HIV disease.

Effects on Other Drugs

Rifabutin induces CYP3A enzymes and therefore may reduce the plasma concentrations of drugs metabolized by those enzymes. This effect may reduce the efficacy of standard doses of such drugs, which include itraconazole, clarithromycin, and saquinavir (see CLINICAL PHARMACOLOGY-Drug-Drug Interactions).

Effects on Rifabutin

Some drugs that inhibit CYP3A may significantly increase the plasma concentration of rifabutin. Because high plasma levels of rifabutin may increase the risk of adverse reactions, carefully monitor patients receiving coadministration of such drugs, which include fluconazole and clarithromycin (see CLINICAL PHARMACOLOGY-Drug-Drug Interactions). In some cases, the dosage of MYCOBUTIN may need to be reduced when it is coadministered with such a drug (see below).

The following table summarizes the results and magnitude of the pertinent drug interactions assessed with rifabutin. The clinical relevance of these interactions and subsequent dose modifications should be judged in light of the population studied, severity of the disease, patient's drug profile, and the likely impact on the risk/benefit ratio.

Rifabutin Interaction Studies [ND - No data AUC - Area under the Concentration vs. Time Curve Cmax - Maximum serum concentration]
Coadministered Drugs | Effect on Rifabutin | Effect on Coadministered Drug | Comments
ANTIVIRALS
Amprenavir | 2.9-fold ↑ AUC, 2.2-fold ↑ Cmax | No significant change in kinetics. | A 50% reduction in the rifabutin dose is recommended when combined with amprenavir. Increased monitoring for adverse reactions is warranted.
Delavirdine | ND | Oral clearance ↑ 5-fold resulting in significantly lower mean trough plasma concentrations (18±15 to 1.0±0.7 µM) | Study conducted in HIV-1 infected patients Rifabutin is not recommended for patients dosed with delavirdine mesylate 400 mg q8h.
Didanosine | No significant change in kinetics. | No significant change in kinetics at steady state.
Fosamprenavir/ritonavir | 64% ↑ AUC [- Drug plus active metabolite] | 35% ↑ AUC and 36% ↑ Cmax, no effect Ctrough (amprenavir) | Dosage reduction of rifabutin by at least 75% (to 150 mg every other day or three times per week) is recommended when combined with fosamprenavir
Indinavir | 204% ↑ in AUC | 32%↓ in AUC
Lopinavir/ritonavir | 5.7-fold ↑ AUC, 3.4 fold ↑ Cmax | No significant change in lopinavir kinetics. | Dosage reduction of rifabutin by at least 75% of the usual dose of 300 mg/day is recommended (i.e., a maximum dose of 150 mg every other day or three times per week). Increased monitoring for adverse reactions is warranted. Further dosage reduction of rifabutin may be necessary.
Saquinavir | ND | 40% ↓ in AUC
Ritonavir | 4 fold increase in AUC, 2.5 fold increase in Cmax | ND | In the presence of ritonavir the subsequent risk of side effects, including uveitis may be increased . If a protease inhibitor is required in a patient treated with rifabutin, agents other than ritonavir should be considered.
Tipranavir/ritonavir[133] | 2.9-fold ↑ AUC, 1.7-fold ↑ Cmax | No significant change in tipranavir kinetics. | Therapeutic drug monitoring of rifabutin is recommended.
Zidovudine | No significant change in kinetics. | Approximately 32%↓ in Cmax and AUC | A large controlled clinical study has shown that these changes are of no clinical relevance.
ANTIFUNGALS
ANTIFUNGALS | 82% ↑ in AUC | No significant change in steady-state plasma concentrations
Itraconazole | ND | 70% to 75% ↓ in Cmax and AUC | One case report suggests a kinetic interaction resulting in an increase in serum rifabutin levels and a risk for developing uveitis in the presence of itraconazole.
Posaconazole | 31%↑ Cmax, 72%↑ AUC | 43%↓ Cmax, 49%↓ AUC | If the drugs are co-administered, patients should be monitored for adverse events associated with rifabutin administration.
Voriconazole | 195%↑ Cmax, 331%↑ AUC [- voriconazole dosed at 400 mg twice daily] | Rifabutin (300 mg once daily) decreased the Cmax and AUC of voriconazole at 200 mg twice daily by 69% and 78%, respectively. During co-administration with rifabutin, the Cmax and AUC of voriconazole at 350 mg twice daily were 96% and 68% of the levels when administered alone at 200 mg twice daily. At a voriconazole dose of 400 mg twice daily Cmax and AUC were 104% and 87% higher, respectively, compared with voriconazole alone at 200 mg twice daily. | If the benefit outweighs the risk, rifabutin may be coadministered with voriconazole if the maintenance dose of voriconazole is increased to 5 mg/kg intravenously every 12 hours or from 200 mg to 350 mg orally, every 12 hours (100 mg to 200 mg orally, every 12 hours in patients less than 40 kg). Careful monitoring of full blood counts and adverse events to rifabutin (e.g. uveitis) is recommended when rifabutin is coadministered with voriconazole
ANTI-PCP (Pneumocystis carinii pneumonia)
Dapsone | ND | Approximately 27% to 40% ↓ in AUC | Study conducted in HIV infected patients (rapid and slow acetylators).
Sulfamethoxazole-Trimethoprim | No significant change in Cmax and AUC | Approximately 15% to 20% ↓ in AUC | In another study, only trimethoprim (not sulfamethoxazole) had 14% ↓ in AUC and 6%↓ in Cmax but were not considered clinically significant.
ANTI-MAC (Mycobacterium avium intracellulare complex)
Azithromycin | No PK interaction | No PK interaction
Clarithromycin | Approximately 77% ↑ in AUC | Approximately 50%↓ in AUC | Study conducted in HIV infected patients. Dose of rifabutin should be adjusted in the presence of clarithromycin
ANTI-TB (Tuberculosis)
Ethambutol | ND | No significant change in AUC or Cmax
Isoniazid | ND | Pharmacokinetics not affected
Pyrazinamide | ND | ND | Study data being evaluated.
OTHER
Methadone | ND | No significant effect | No apparent effect of rifabutin on either peak levels of methadone or systemic exposure based upon AUC. Rifabutin kinetics not evaluated.
Ethinylestradiol | ND | 35%↓ AUC 20%↓ Cmax | Patients should be advised to use other methods of contraception.
Norethindrone | ND | 46%↓ AUC | Patients should be advised to use other methods of contraception.
Tacrolimus | ND | ND | Authors report that rifabutin decreases tacrolimus trough blood levels.
Theophylline | ND | No significant change in AUC or Cmax compared with baseline.

Other drugs

The structurally similar drug, rifampin, is known to reduce the plasma concentrations of a number of other drugs (see prescribing information for rifampin). Although rifabutin is a weaker enzyme inducer than rifampin, it may be expected to have some effect on those drugs as well.

Carcinogenesis, Mutagenesis, Impairment of Fertility

Long-term carcinogenicity studies were conducted with rifabutin in mice and in rats. Rifabutin was not carcinogenic in mice at doses up to 180 mg/kg/day, or approximately 36 times the recommended human daily dose. Rifabutin was not carcinogenic in the rat at doses up to 60 mg/kg/day, about 12 times the recommended human dose.

Rifabutin was not mutagenic in the bacterial mutation assay (Ames Test) using both rifabutin-susceptible and resistant strains. Rifabutin was not mutagenic in Schizosaccharomyces pombe P1 and was not genotoxic in V-79 Chinese hamster cells, human lymphocytes in vitro, or mouse bone marrow cells in vivo.

Fertility was impaired in male rats given 160 mg/kg (32 times the recommended human daily dose).

Pregnancy

There are no adequate and well-controlled studies in pregnant or breastfeeding women.

Pregnancy Category B

Reproduction studies have been carried out in rats and rabbits given rifabutin using dose levels up to 200 mg/kg (40 times the recommended human daily dose). No teratogenicity was observed in either species. In rats, given 200 mg/kg/day, there was a decrease in fetal viability. In rats, at 40 mg/kg/day (8 times the recommended human daily dose), rifabutin caused an increase in fetal skeletal variants. In rabbits, at 80 mg/kg/day (16 times the recommended human daily dose), rifabutin caused maternotoxicity and increase in fetal skeletal anomalies. There are no adequate and well-controlled studies in pregnant women. Because animal reproduction studies are not always predictive of human response, rifabutin should be used in pregnant women only if the potential benefit justifies the potential risk to the fetus.

Nursing Mothers

It is not known whether rifabutin is excreted in human milk. Because many drugs are excreted in human milk and because of the potential for serious adverse reactions in nursing infants, a decision should be made whether to discontinue nursing or discontinue the drug, taking into account the importance of the drug to the mother.

Pediatric Use

Safety and effectiveness of rifabutin for prophylaxis of MAC in children have not been established. Limited safety data are available from treatment use in 22 HIV-positive children with MAC who received MYCOBUTIN in combination with at least two other antimycobacterials for periods from 1 to 183 weeks. Mean doses (mg/kg) for these children were: 18.5 (range 15.0 to 25.0) for infants one year of age, 8.6 (range 4.4 to 18.8) for children 2 to 10 years of age, and 4.0 (range 2.8 to 5.4) for adolescents 14 to 16 years of age. There is no evidence that doses greater than 5 mg/kg daily are useful. Adverse experiences were similar to those observed in the adult population, and included leukopenia, neutropenia, and rash. In addition, corneal deposits have been observed in some patients during routine ophthalmologic surveillance of HIV-positive pediatric patients receiving MYCOBUTIN as part of a multiple-drug regimen for MAC prophylaxis. These are tiny, almost transparent, asymptomatic peripheral and central corneal deposits which do not impair vision. Doses of MYCOBUTIN may be administered mixed with foods such as applesauce.

Geriatric Use

Clinical studies of MYCOBUTIN did not include sufficient numbers of subjects aged 65 and over to determine whether they respond differently from younger subjects. Other reported clinical experience has not identified differences in responses between the elderly and younger patients. In general, dose selection for an elderly patient should be cautious, usually starting at the low end of the dosing range, reflecting the greater frequency of decreased hepatic, renal, or cardiac function, and of concomitant disease or other drug therapy (see CLINICAL PHARMACOLOGY).

ADVERSE REACTIONS

MYCOBUTIN Capsules were generally well tolerated in the controlled clinical trials. Discontinuation of therapy due to an adverse event was required in 16% of patients receiving MYCOBUTIN, compared to 8% of patients receiving placebo in these trials. Primary reasons for discontinuation of MYCOBUTIN were rash (4% of treated patients), gastrointestinal intolerance (3%), and neutropenia (2%).

The following table enumerates adverse experiences that occurred at a frequency of 1% or greater, among the patients treated with MYCOBUTIN in studies 023 and 027.

CLINICAL ADVERSE EXPERIENCES REPORTED IN ≥1% OF PATIENTS TREATED WITH MYCOBUTIN
ADVERSE EVENT | MYCOBUTIN (n = 566) % | PLACEBO (n = 580) %
BODY AS A WHOLE
Abdominal Pain | 4 | 3
Asthenia | 1 | 1
Chest Pain | 1 | 1
Fever | 2 | 1
Headache | 3 | 5
Pain | 1 | 2
DIGESTIVE SYSTEM
Anorexia | 2 | 2
Diarrhea | 3 | 3
Dyspepsia | 3 | 1
Eructation | 3 | 1
Flatulence | 2 | 1
Nausea | 6 | 5
Nausea and Vomiting | 3 | 2
Vomiting | 1 | 1
MUSCULOSKELETAL SYSTEM
Myalgia | 2 | 1
NERVOUS SYSTEM
Insomnia | 1 | 1
SKIN AND APPENDAGES
Rash | 11 | 8
SPECIAL SENSES
Taste Perversion | 3 | 1
UROGENITAL SYSTEM
Discolored Urine | 30 | 6

CLINICAL ADVERSE EVENTS REPORTED IN <1% OF PATIENTS WHO RECEIVED MYCOBUTIN

Considering data from the 023 and 027 pivotal trials, and from other clinical studies, MYCOBUTIN appears to be a likely cause of the following adverse events which occurred in less than 1% of treated patients: flu-like syndrome, hepatitis, hemolysis, arthralgia, myositis, chest pressure or pain with dyspnea, and skin discoloration.

The following adverse events have occurred in more than one patient receiving MYCOBUTIN, but an etiologic role has not been established: seizure, paresthesia, aphasia, confusion, and non-specific T wave changes on electrocardiogram.

When MYCOBUTIN was administered at doses from 1050 mg/day to 2400 mg/day, generalized arthralgia and uveitis were reported. These adverse experiences abated when MYCOBUTIN was discontinued.

The following table enumerates the changes in laboratory values that were considered as laboratory abnormalities in studies 023 and 027.

PERCENTAGE OF PATIENTS WITH LABORATORY ABNORMALITIES
LABORATORY ABNORMALITIES | MYCOBUTIN (n = 566) % | PLACEBO (n = 580) %
Chemistry:
Increased Alkaline Phosphatase [all values >450 U/L] | < 1 | 3
Increased SGOT [all values >150 U/L] | 7 | 12
Increased SGPT | 9 | 11
Hematology:
Anemia [all hemoglobin values < 8.0 g/dL] | 6 | 7
Eosinophilia | 1 | 1
Leukopenia [all WBC values < 1,500/mm ^3] | 17 | 16
Neutropenia [all ANC values < 750/mm ^3] | 25 | 20
Thrombocytopenia [all platelet count values < 50,000/mm ^3] | 5 | 4
INCLUDES GRADE 3 OR 4 TOXICITIES AS SPECIFIED:

The incidence of neutropenia in patients treated with MYCOBUTIN was significantly greater than in patients treated with placebo (p = 0.03). Although thrombocytopenia was not significantly more common among patients treated with MYCOBUTIN in these trials, MYCOBUTIN has been clearly linked to thrombocytopenia in rare cases. One patient in study 023 developed thrombotic thrombocytopenic purpura, which was attributed to MYCOBUTIN.

Uveitis is rare when MYCOBUTIN is used as a single agent at 300 mg/day for prophylaxis of MAC in HIV-infected persons, even with the concomitant use of fluconazole and/or macrolide antibiotics. However, if higher doses of MYCOBUTIN are administered in combination with these agents, the incidence of uveitis is higher.

Patients who developed uveitis had mild to severe symptoms that resolved after treatment with corticosteroids and/or mydriatic eye drops; in some severe cases, however, resolution of symptoms occurred after several weeks.

When uveitis occurs, temporary discontinuance of MYCOBUTIN and ophthalmologic evaluation are recommended. In most mild cases, MYCOBUTIN may be restarted; however, if signs or symptoms recur, use of MYCOBUTIN should be discontinued (Morbidity and Mortality Weekly Report, September 9, 1994).

Adverse reactions identified through clinical trials or post-marketing surveillance by system organ class (SOC) are listed below.

Blood and lymphatic system disorders: Pancytopenia, white blood cell disorders (including agranulocytosis, leukopenia, lymphopenia, granulocytopenia, neutropenia, white blood cell count decreased, neutrophil count decreased), thrombocytopenia, platelet count decreased, anemia.

Immune system disorders: Shock, hypersensitivity, bronchospasm, rash, eosinophilia.

Eye disorders: Uveitis, corneal deposits.

Gastrointestinal disorders: Clostridium difficile colitis , nausea, vomiting.

Hepato-biliary disorders: Jaundice, hepatic enzyme increased.

Skin and subcutaneous tissue disorders: Skin discoloration.

Musculoskeletal and connective tissue disorders: Arthralgia, myalgia.

General disorders and administration site conditions: Pyrexia.

Pyrexia, rash and rarely other hypersensitivity reactions such as eosinophilia, bronchospasm and shock might occur, as has been seen with other antibiotics. A limited number of skin discoloration has been reported. Mild to severe, reversible uveitis has been reported less frequently when MYCOBUTIN is used at 300 mg as monotherapy in MAC prophylaxis versus MYCOBUTIN in combination with clarithromycin for MAC treatment (see also WARNINGS). Corneal deposits have been reported during routine ophthalmologic surveillance of some HIV-positive pediatric patients receiving MYCOBUTIN as part of a multiple drug regimen for MAC prophylaxis. The deposits are tiny, almost transparent, asymptomatic peripheral and central corneal deposits, and do not impair vision.

ANIMAL TOXICOLOGY

Liver abnormalities (increased bilirubin and liver weight) occurred in all species tested, in rats at doses 5 times, in monkeys at doses 8 times, and in mice at doses 6 times the recommended human daily dose. Testicular atrophy occurred in baboons at doses 4 times the recommended human dose, and in rats at doses 40 times the recommended human daily dose.

OVERDOSAGE

No information is available on accidental overdosage in humans.

Treatment

While there is no experience in the treatment of overdose with MYCOBUTIN Capsules, clinical experience with rifamycins suggests that gastric lavage to evacuate gastric contents (within a few hours of overdose), followed by instillation of an activated charcoal slurry into the stomach, may help absorb any remaining drug from the gastrointestinal tract.

Rifabutin is 85% protein bound and distributed extensively into tissues (Vss:8 to 9 L/kg). It is not primarily excreted via the urinary route (less than 10% as unchanged drug); therefore, neither hemodialysis nor forced diuresis is expected to enhance the systemic elimination of unchanged rifabutin from the body in a patient with an overdose of MYCOBUTIN.

DOSAGE AND ADMINISTRATION

It is recommended that MYCOBUTIN Capsules be administered at a dose of 300 mg once daily. For those patients with propensity to nausea, vomiting, or other gastrointestinal upset, administration of MYCOBUTIN at doses of 150 mg twice daily taken with food may be useful. For patients with severe renal impairment (creatinine clearance less than 30 mL/min), the dose of MYCOBUTIN should be reduced by 50%. No dosage adjustment is required for patients with mild to moderate renal impairment. Reduction of the dose of MYCOBUTIN may also be needed for patients receiving concomitant treatment with certain other drugs (see PRECAUTIONS-Drug Interactions).

HOW SUPPLIED

MYCOBUTIN Capsules (rifabutin capsules, USP) are supplied as hard gelatin capsules having an opaque red-brown cap and body, imprinted with MYCOBUTIN/PHARMACIA & UPJOHN in white ink, each containing 150 mg of rifabutin, USP.

MYCOBUTIN is available as follows:

Bottles of 10 | NDC 54868-2841-3
Bottles of 30 | NDC 54868-2841-4
Bottles of 50 | NDC 54868-2841-0
Bottles of 60 | NDC 54868-2841-1
Bottles of 100 | NDC 54868-2841-2

STORAGE AND HANDLING

Keep tightly closed and dispense in a tight container as defined in the USP. Store at 25°C (77°F); excursions permitted to 15°–30°C (59°–86°F) [see USP Controlled Room Temperature].

Rx only

LAB-0217-4.0

January 2010

Relabeling and Repackaging by:
Physicians Total Care, Inc.
Tulsa, OK 74146

PRINCIPAL DISPLAY PANEL - 150 mg Capsule Label

Mycobutin®
rifabutin capsules, USP

150 mg

Rx only